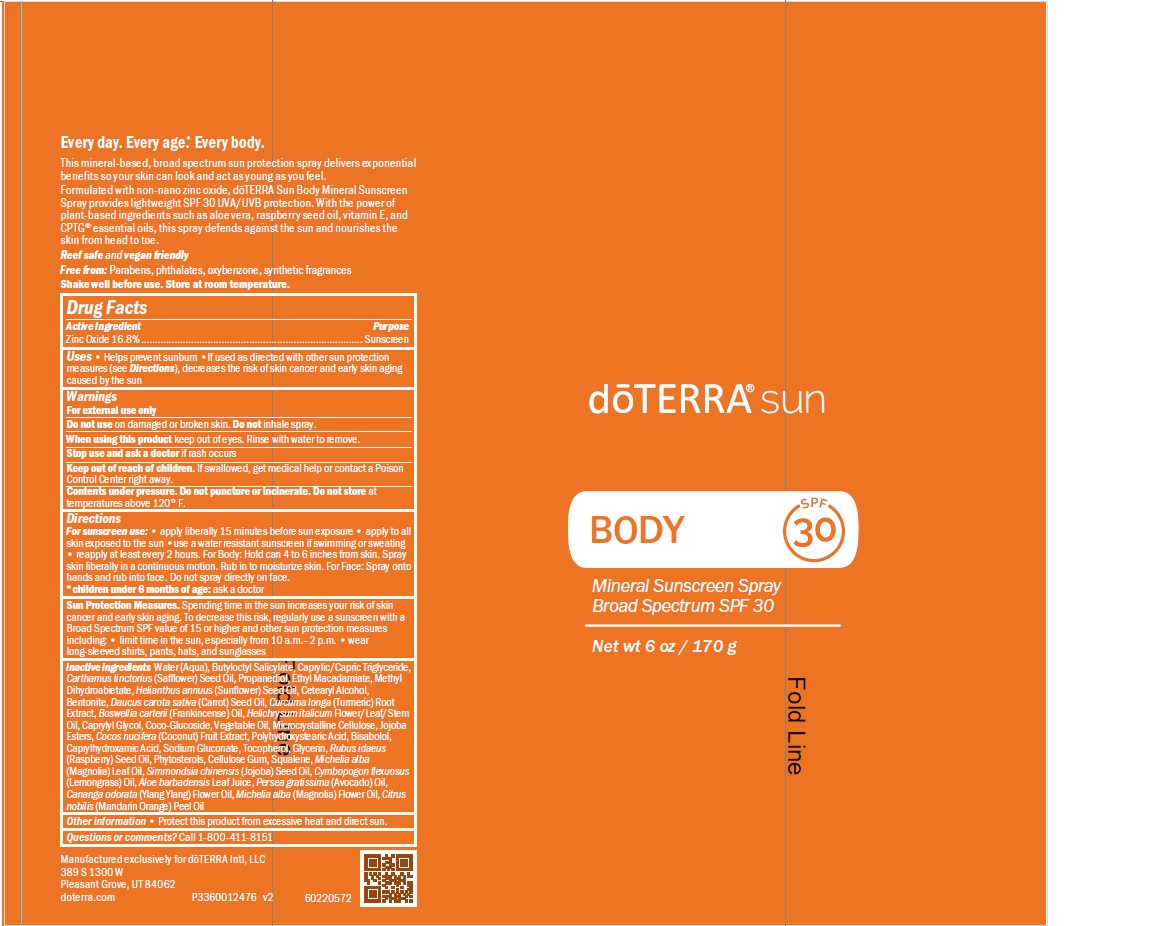 DRUG LABEL: doTERRA sun
NDC: 71630-173 | Form: SPRAY
Manufacturer: doTERRA International, LLC
Category: otc | Type: HUMAN OTC DRUG LABEL
Date: 20250128

ACTIVE INGREDIENTS: ZINC OXIDE 17.5 g/100 g
INACTIVE INGREDIENTS: SODIUM GLUCONATE; RASPBERRY SEED OIL; ALOE VERA LEAF; AVOCADO OIL; YLANG-YLANG OIL; TOCOPHEROL; BUTYLOCTANOL; SQUALENE; MICHELIA ALBA LEAF OIL; EAST INDIAN LEMONGRASS OIL; TURMERIC OIL; HELICHRYSUM ITALICUM FLOWER OIL; .BETA.-BISABOLOL; PROPANEDIOL; METHYL DIHYDROABIETATE; SIMMONDSIA CHINENSIS SEED; FRANKINCENSE OIL; BENTONITE; MICROCRYSTALLINE CELLULOSE; MANDARIN OIL; CAPRYLHYDROXAMIC ACID; COCO GLUCOSIDE; SUNFLOWER OIL; CETOSTEARYL ALCOHOL; CAPRYLYL GLYCOL; HYDROLYZED JOJOBA ESTERS (ACID FORM); COCONUT; MALIC ACID; POLYHYDROXYSTEARIC ACID (2300 MW); GLYCERIN; CAPRYLIC/CAPRIC ACID; SAFFLOWER OIL; BUTYLOCTYL SALICYLATE; WATER; ETHYL MACADAMIATE; CARROT SEED OIL

doTERRA Sun Body Mineral Sunscreen Spray

Active ingredient(s) Zinc Oxide 16.4%

PURPOSE

Sunscreen

INDICATIONS AND USAGE

helps prevent sunburn, if used as directed with othe rsn protection measures, decreases the risk of skin cancer and early skin aging caused by the sun

WARNINGS

For external use only
Do not use on damaged or broken skin
When using this product keep out of eyes. Rinse with water to remove.
Stop use and ask a doctor if rash occurs
Keep out of reach of children. If swallowed, get medical help or contact a
Poison Control Center right away.

WHEN USING

For sunscreen use: • apply liberally 15 minutes before sun exposure • apply
to all skin exposed to the sun •use a water resistant sunscreen if swimming or
sweating • reapply at least every 2 hours.
*children under 6 months of age: ask a doctor

Stop use and ask a doctor if rash occurs

Keep out of reach of children. If swallowed, get medical help or contact a
Poison Control Center right away.

Directions

For sunscreen use: • apply liberally 15 minutes before sun exposure • apply
to all skin exposed to the sun •use a water resistant sunscreen if swimming or
sweating • reapply at least every 2 hours.

Other information

protect this product from excessive heat and direct sun.protect this product from excessive heat and direct sun.

Inactive Ingredients

Water (Aqua), Butyloctyl Salicylate, Caprylic/Capric
Triglyceride, Carthamus tinctorius (Safflower) Seed Oil, Propanediol, Ethyl
Macadamiate, Methyl Dihydroabietate, Helianthus annuus (Sunflower) Seed Oil,
Cetearyl Alcohol, Bentonite, Daucus carota sativa (Carrot) Seed Oil, Curcuma
longa (Turmeric) Root Extract, Boswellia carterii (Frankincense) Oil, Helichrysum
italicum Flower/Leaf/Stem Oil, Caprylyl Glycol, Coco-Glucoside, Vegetable Oil,
Microcrystalline Cellulose, Jojoba Esters, Cocos nucifera (Coconut) Fruit Extract,
Polyhydroxystearic Acid, Bisabolol, Caprylhydroxamic Acid, Sodium Gluconate,
Tocopherol, Glycerin, Rubus idaeus (Raspberry) Seed Oil, Phytosterols, Cellulose
Gum, Squalene, Michelia alba (Magnolia) Leaf Oil, Simmondsia chinensis
(Jojoba) Seed Oil, Cymbopogon flexuosus (Lemongrass) Oil, Aloe barbadensis
Leaf Juice, Persea gratissima (Avocado) Oil, Cananga odorata (Ylang Ylang) Flower
Oil, Michelia alba (Magnolia) Flower Oil, Citrus nobilis (Mandarin Orange) Peel Oil

Principle Display Panel

Mineral Sunscreen Spray Broad Spectrum Spray SPF 30